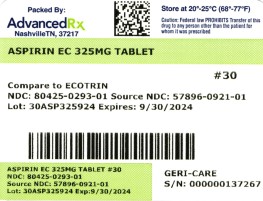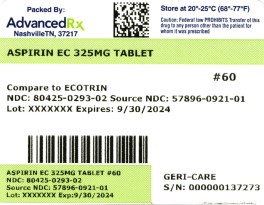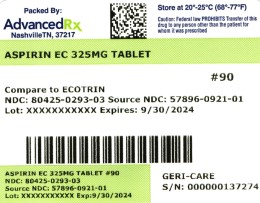 DRUG LABEL: Aspirin
NDC: 80425-0293 | Form: TABLET, COATED
Manufacturer: Advanced Rx Pharmacy of Tennessee, LLC
Category: otc | Type: HUMAN OTC DRUG LABEL
Date: 20241231

ACTIVE INGREDIENTS: ASPIRIN 325 mg/1 1
INACTIVE INGREDIENTS: FERROSOFERRIC OXIDE; CELLULOSE, MICROCRYSTALLINE

Aspirin Tablet

Active Ingredient (in each tablet)

Aspirin 325 mg(NSAID)*
*nonsteroidal anti-inflammatory drug

PURPOSE

Pain reliever

INDICATIONS AND USAGE

temporarily relieves minor aches and pains due to:
headache
muscle pain
toothache
menstrual pain
colds
minor pains of arthritis
temporarily reduces fever

Warnings

Reye's Syndrome: Children and teenagers who have or are recovering from chicken pox or flu-like symptoms should not use this product. When using this product, if changes in behavior with nausea and vomiting occur, consult a doctor because these symptoms could be an early sign of Reye's syndrome, a rare but serious illness.

Allergy Alert: Aspirin may cause a severe allergic reaction which may include:

- hives
- facial swelling
- asthma (wheezing)
- shock

Stomach bleeding warning:

This product contains an NSAID, which may cause severe stomach bleeding. The chance is higher if you:

- are age 60 or older
- have had stomach ulcers or bleeding problems
- take a blood thinning (anticoagulant) or steroid drug
- take other drugs containing prescription or nonprescription NSAIDs (aspirin, ibuprofen, naproxen, or others)
- have 3 or more alcoholic drinks every day while using this product
- take more or for a longer time than directed

Do not use if you are allergic to aspirin or any other pain reliever/fever reducer.

Ask a doctor before use if

- the stomach bleeding warning applies to you
- you are taking a diuretic
- you have a history of stomach problems, such as heartburn
- you have: -high blood pressure -heart disease -liver cirrhosis -kidney disease -asthma

Ask a doctor or pharmacist before use if you are

- taking any other drug containing an NSAID (prescription or nonprescription)
- taking a blood thinning (anticoagulant) or steroid drug
- taking a prescription drug for diabetes, gout or arthritis

Stop use and ask a doctor if

- you experience any of the following signs of stomach bleeding: -feel faint -vomit blood -have bloody or black stools -have stomach pain that does not get better
- an allergic reaction occurs. Seek medical help right away
- pain gets worse or lasts more than 10 days
- redness or swelling is present
- fever gets worse or lasts more than 3 days
- any new symptoms occur
- ringing in the ears or loss of hearing occurs

If pregnant or breast-feeding,

ask a health professional before use. It is especially important not to use aspirin during the last 3 months of pregnancy unless definitely directed to do so by a doctor because it may cause problems in the unborn child or complications during delivery.

Keep out of reach of children. In case of overdose, get medical help or contact a Poison Control Center right away.

Directions
• drink a full glass of water with each dose
• adults and children 12 years and over: take 1 to 2 tablets every 4 hours while symptoms last. Do not take more than 12 tablets in 24 hours unless directed by a doctor
• children under 12 years: consult a doctor

Directions

- drink a full glass of water with each dose
- swallow whole, do not chew or crush
- do not exceed recommended dose
- adults and children 12 years and older: take 1-2 tablets every 4 hours, as needed, not more than 12 tablets in 24 hours, or as directed by a doctor
- children under 12 years: ask a doctor

Keep out of reach of children. In case of overdose, get medical help or contact a Poison Control Center right away (1-800-222-1222).

Other Information

store at 20°C - 25°C (68°F - 77°F); excursions permitted between 15°C - 30°C (59°F - 86°F)

INACTIVE INGREDIENT

black iron oxide, cellulose, corn starch, D&C yellow #10 lake, FD&C yellow #6 lake, hypromellose, polydextrose,
polyethylene glycol, polyvinyl acetate phthalate, propylene glycol, shellac wax, silicon dioxide, simethicone, sodium alginate, sodium bicarbonate, stearic acid, talc, titanium dioxide, triacetin, triethyl citrate.

QUESTIONS

Manufacturer: 1-800-540-3765

Other information

store at 25°C (77°F) excursions permitted between 15°-30°C (59°-86°F)
use by expiration date on package

Stop use and ask a doctor if

- you experience any of the following signs of stomach bleeding:
  - feel faint
  - have bloody or black stools
  - vomit blood
  - have stomach pain that does not get better
- pain gets worse or lasts more than 10 days
- fever gets worse or lasts more than 3 days
- redness or swelling is present in the painful area
- any new symptoms appear
- ringing in the ears or a loss of hearing occurs